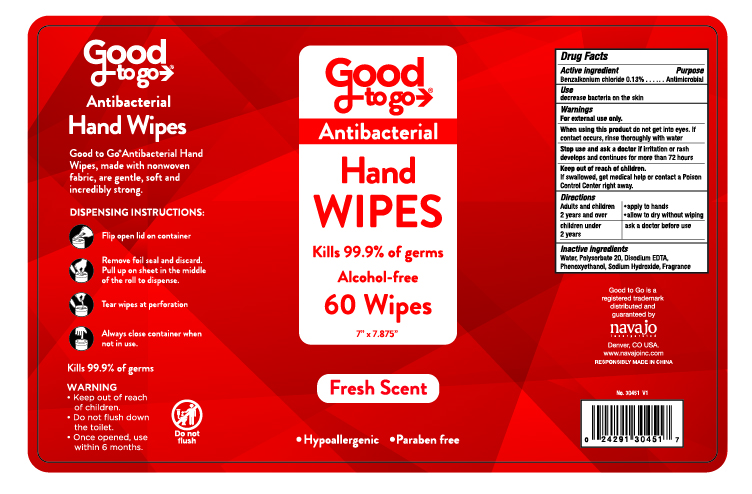 DRUG LABEL: Good To Go Antibacterial Wipes
NDC: 67751-205 | Form: SWAB
Manufacturer: Navajo Manufacturing Company Inc.
Category: otc | Type: HUMAN OTC DRUG LABEL
Date: 20201110

ACTIVE INGREDIENTS: BENZALKONIUM CHLORIDE 0.13 1/100 1
INACTIVE INGREDIENTS: WATER; POLYSORBATE 20; PHENOXYETHANOL; EDETATE DISODIUM ANHYDROUS; FRAGRANCE LEMON ORC2001060; SODIUM HYDROXIDE

Good To Go Antibacterial Wipes

Active Ingredient

Benzalkonium Chloride 0.13%

Purpose

Antimicrobial

Use

descrease bacteria on the skin.

Warnings

For external use only.

When using this product do not get into eyes. If contact occurs, rinse thoroughly with water.

Stop use and ask a doctor if irritation or rash develops and continues for more than 72 hours.

Keep out of reach of children. If swallowed, get medical help or contact a Poison Control Center right away.

Directions

Adults and children 2 years and over | - apply to hands - allow to dry without wiping
children under 2 years | ask a doctor before use

Inactive ingredients

Water, Polysorbate 20, Disodium EDTA, Phenoxyethanol, Sodium Hydroxide, Fragrance.